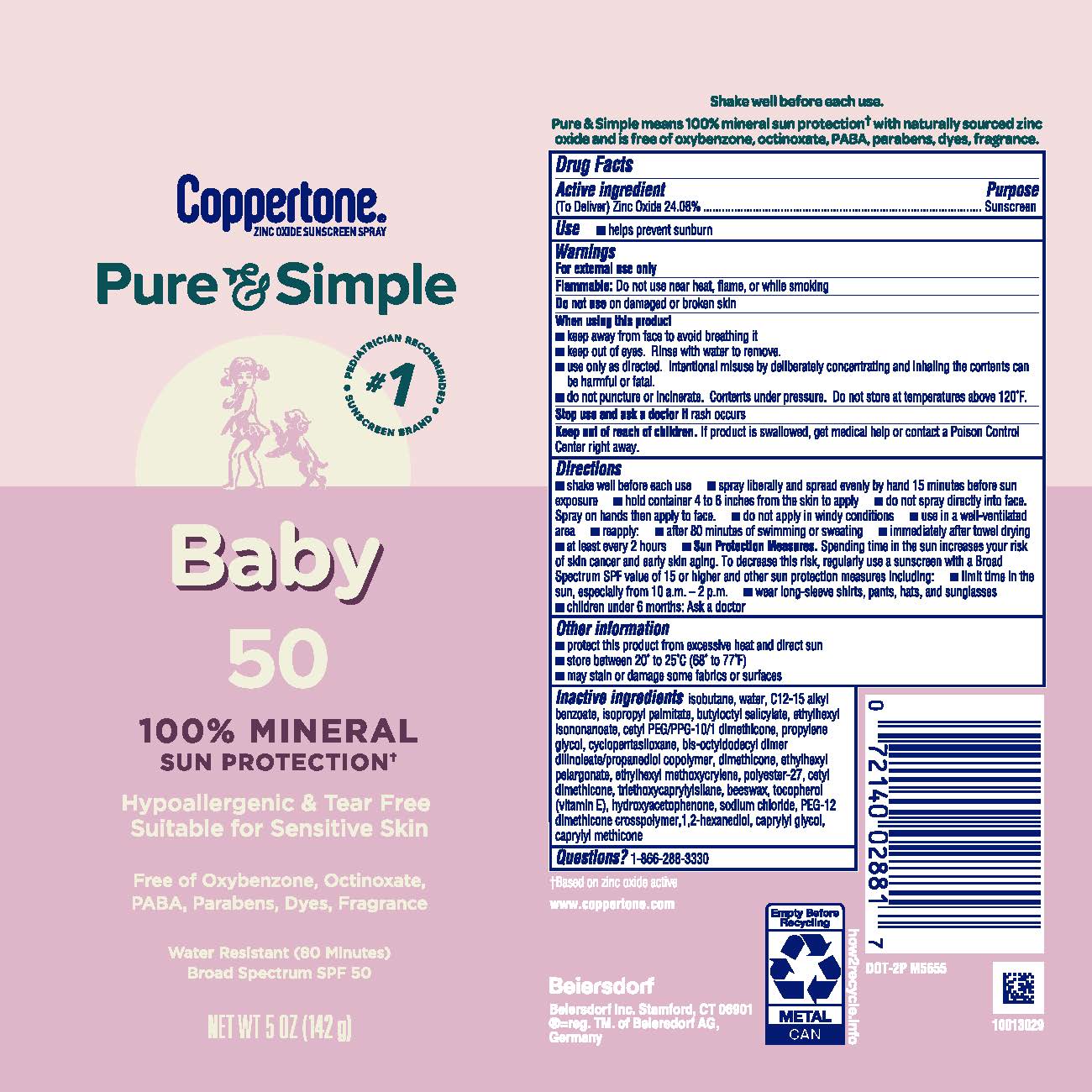 DRUG LABEL: Coppertone Pure and Simple Baby Sunscreen SPF 50
NDC: 66800-2881 | Form: AEROSOL, SPRAY
Manufacturer: Beiersdorf Inc
Category: otc | Type: HUMAN OTC DRUG LABEL
Date: 20251231

ACTIVE INGREDIENTS: ZINC OXIDE 24.08 g/100 g
INACTIVE INGREDIENTS: ISOBUTANE; ETHYLHEXYL ISONONANOATE; WATER; CETYL PEG/PPG-10/1 DIMETHICONE (HLB 2); CAPRYLYL TRISILOXANE; DIMETHICONE; CAPRYLYL GLYCOL; ALKYL (C12-15) BENZOATE; BUTYLOCTYL SALICYLATE; PROPYLENE GLYCOL; PEG-12 DIMETHICONE; ETHYLHEXYL METHOXYCRYLENE; CETYL DIMETHICONE 150; HYDROXYACETOPHENONE; ISOPROPYL PALMITATE; TOCOPHEROL; CYCLOMETHICONE 5; TRIETHOXYCAPRYLYLSILANE; SYNTHETIC BEESWAX; 1,2-HEXANEDIOL; POLYESTER-7; BIS-OCTYLDODECYL DIMER DILINOLEATE/PROPANEDIOL COPOLYMER; ETHYLHEXYL PELARGONATE; SODIUM CHLORIDE

P&S Baby Spray SPF 50

Active ingredient

Zinc Oxide (24.08%)

Purpose

Sunscreen

Uses

■ helps prevent sunburn

Warnings

For external use only
Flammable:Do not use near heat, flame, or while smoking

Do not useon damaged or broken skin

When using this product
■ keep away from face to avoid breathing it

■ keep out of eyes. Rinse with water to remove.

■ use only as directed. Intentional misuse by deliberately concentrating and inhaling the contents can be harmful or fatal.

■ do not puncture or incinerate. Contents under pressure. Do not store at temperatures above 120˚F.

Stop use and ask a doctor ifrash occurs

Keep out of reach of children.If product is swallowed, get medical help or contact a Poison Control Center right away.

Directions

■ shake well before each use

■ spray liberally and spread evenly by hand 15 minutes before sun exposure

■ hold container 4 to 6 inches from the skin to apply

■ do not spray directly into face. Spray on hands then apply to face.

■ do not apply in windy conditions

■ use in a well-ventilated area

■ reapply:

■ after 80 minutes of swimming or sweating

■ immediately after towel drying

■ at least every 2 hours

■ Sun Protection Measures.Spending time in the sun increases your risk of skin cancer and early skin aging. To decrease this risk, regularly use a sunscreen with a Broad Spectrum SPF value of 15 or higher and other sun protection measures including:

■ limit time in the sun, especially from 10 a.m. – 2 p.m.

■ wear long-sleeve shirts, pants, hats, and sunglasses

■ children under 6 months: Ask a doctor

Other information

■ protect this product from excessive heat and direct sun

■ store between 20˚ to 25˚C (68˚ to 77˚F)

■ may stain or damage some fabrics or surfaces

Inactive ingredients

isobutane, water, C12-15 alkyl benzoate, isopropyl palmitate, butyloctyl salicylate, ethylhexyl isononanoate, cetyl PEG/PPG-10/1 dimethicone, propylene glycol, cyclopentasiloxane, bis-octyldodecyl dimer dilinoleate/propanediol copolymer, dimethicone, ethylhexyl pelargonate, ethylhexyl methoxycrylene, polyester-27, cetyl dimethicone, triethoxycaprylylsilane, beeswax, tocopherol (vitamin E), hydroxyacetophenone, sodium chloride, PEG-12 dimethicone crosspolymer, 1,2-hexanediol, caprylyl glycol, caprylyl methicone

Questions?

1-866-288-3330

PACKAGE LABEL

Coppertone

Zinc Oxide Sunscreen Spray

Pure&Simple

#1 Pediatrician Recommended Sunscreen Spray

Baby

50

100% Mineral Sun Protection

Hypoallergenic & Tear Free

Suitable for Sensitive Skin

Free of Oxybenzone, Octinoxate, PABA, Parabens, Dyes, Fragreance

Water Resistant (80 Minutes)

Broad Spectrum SPF 50